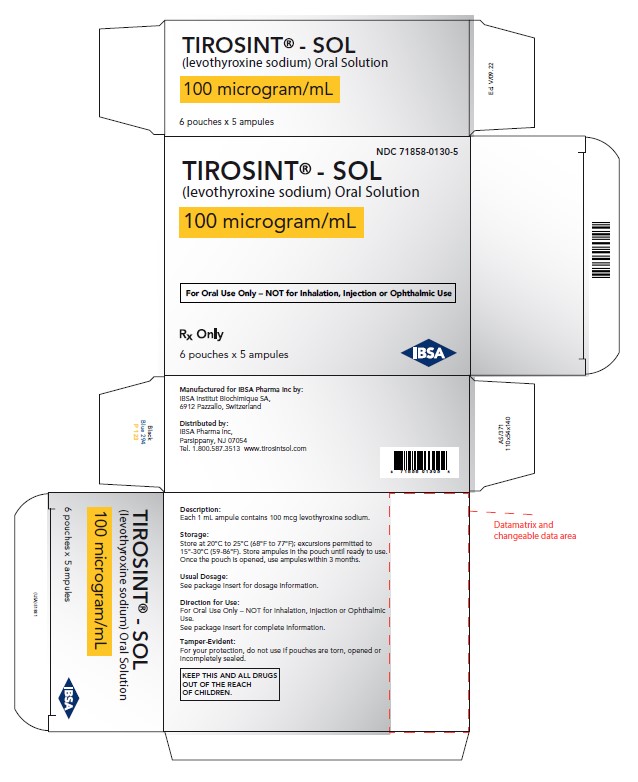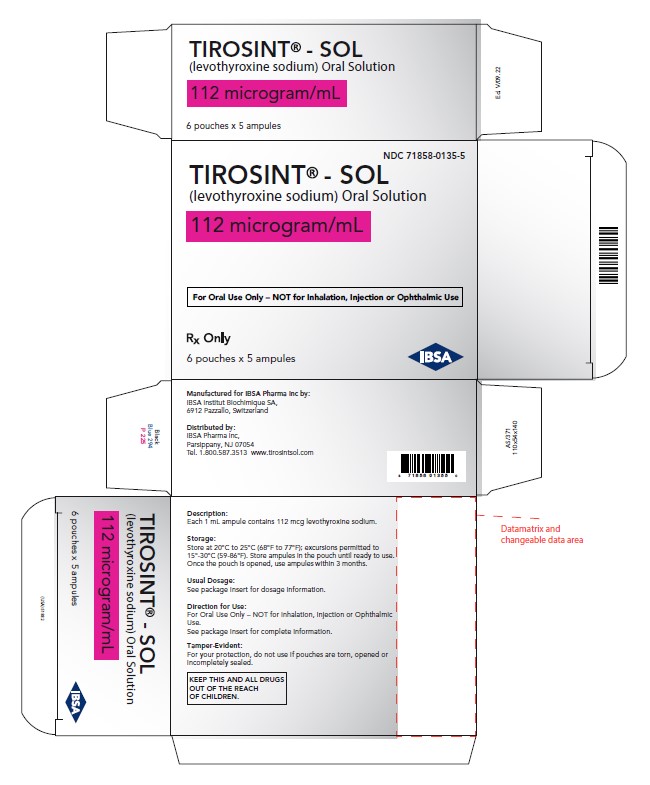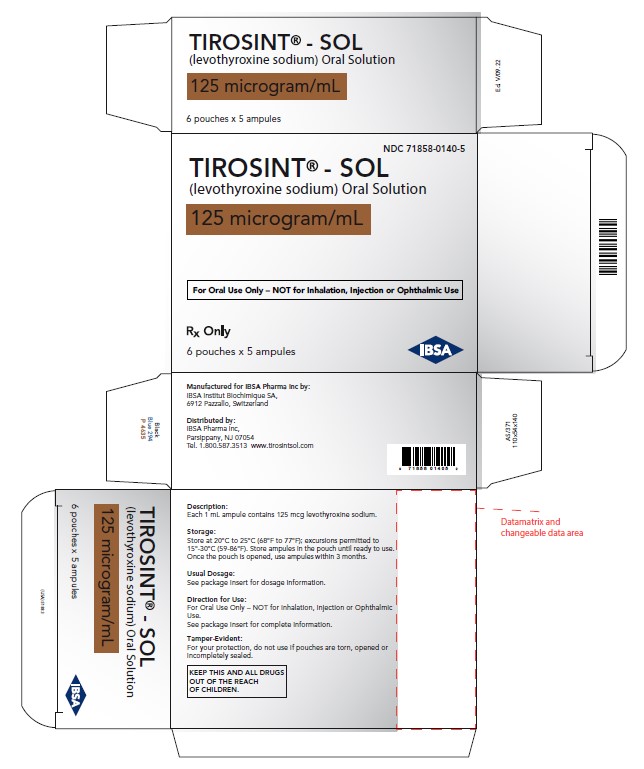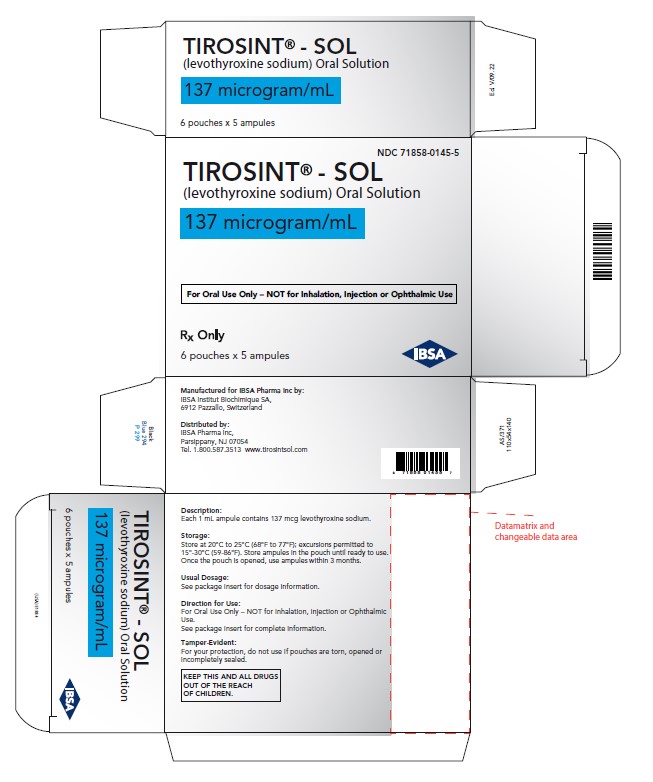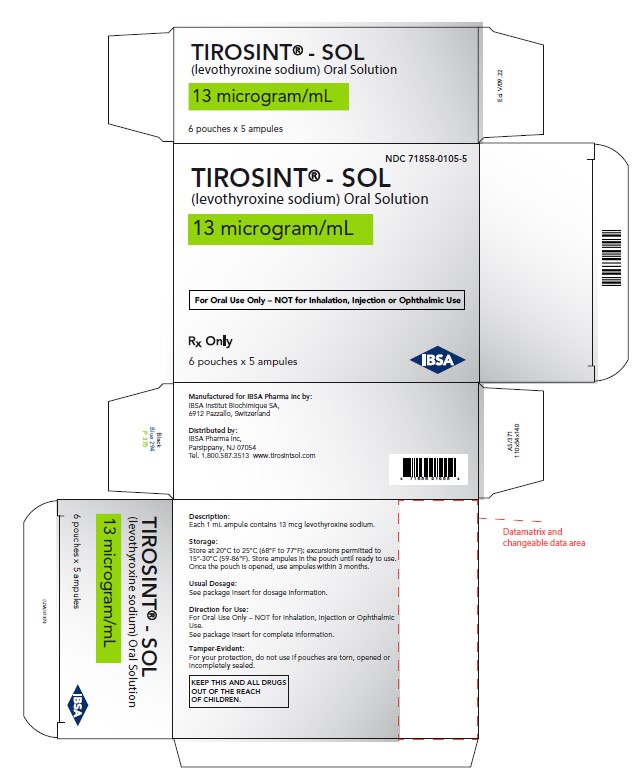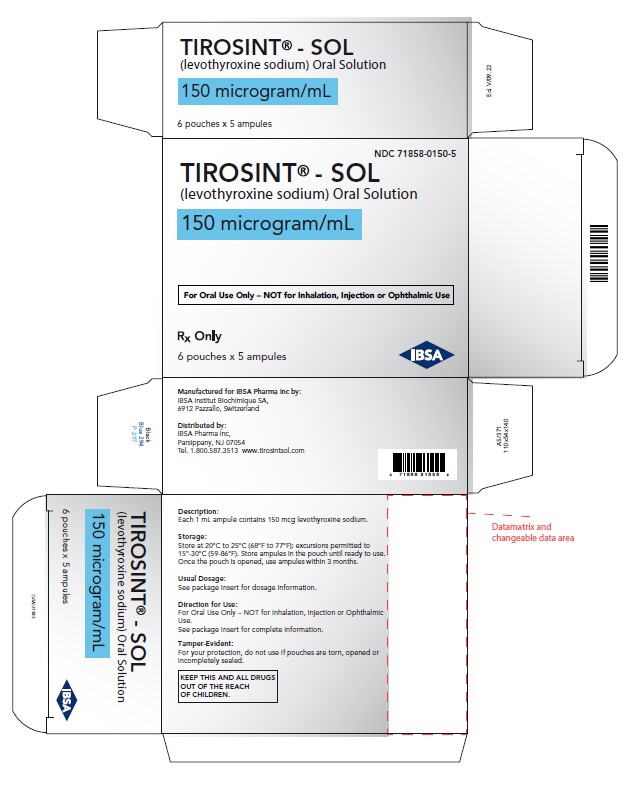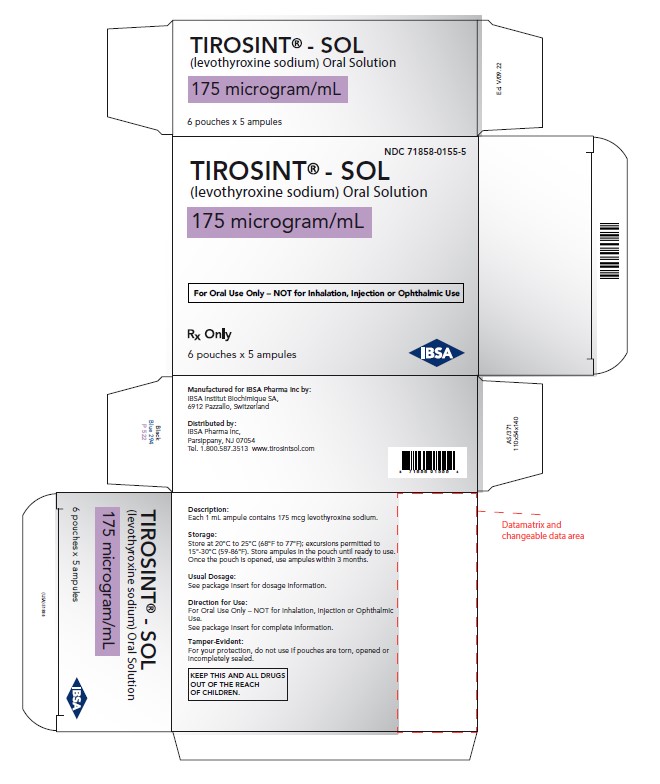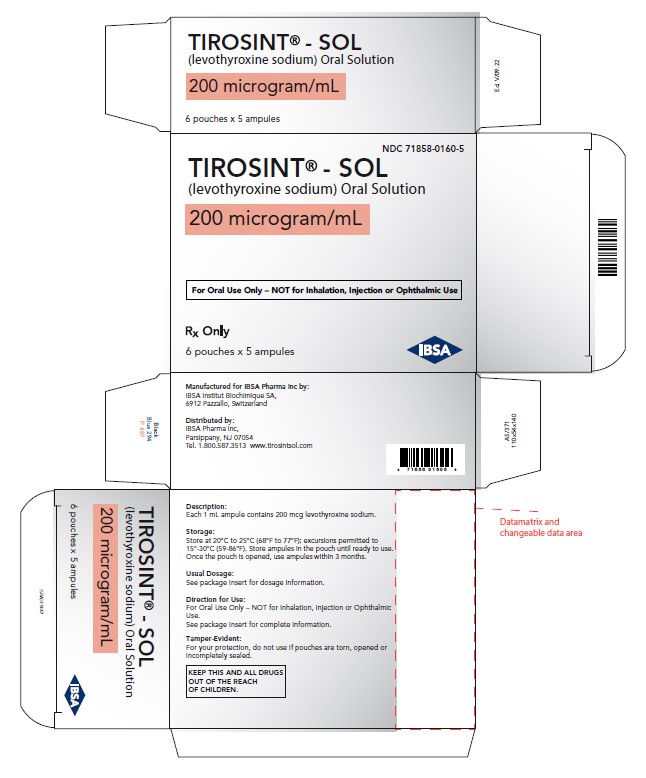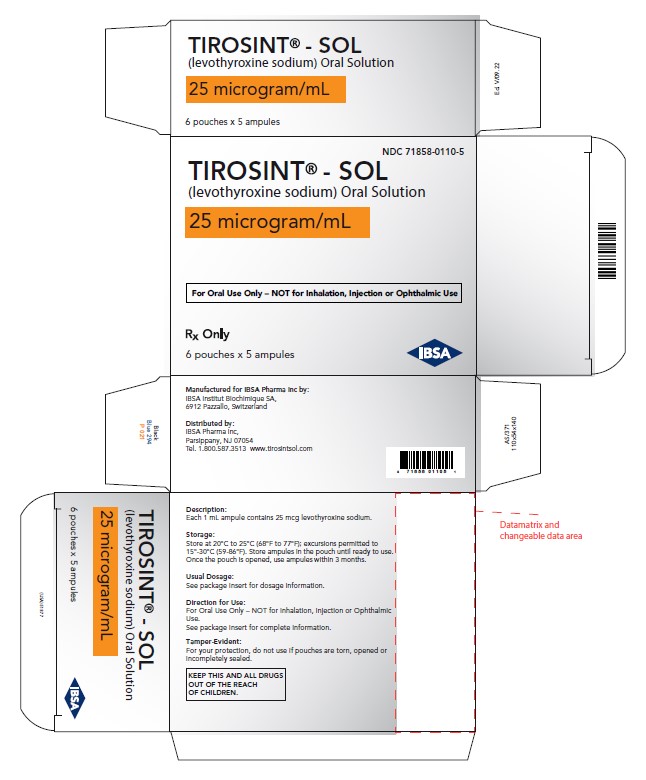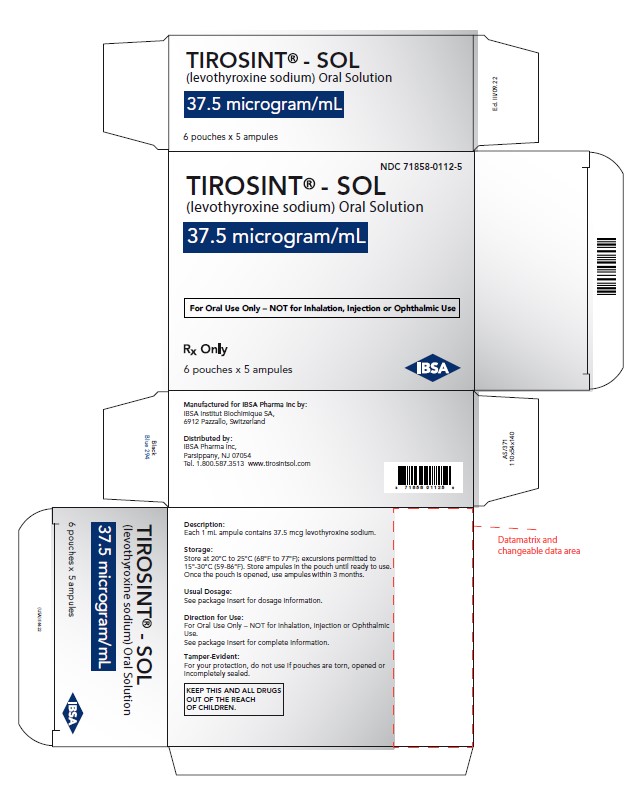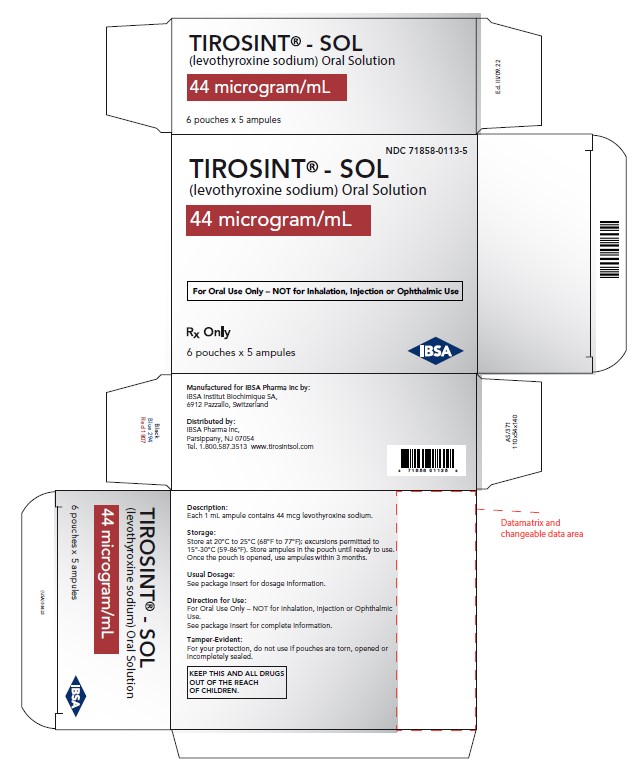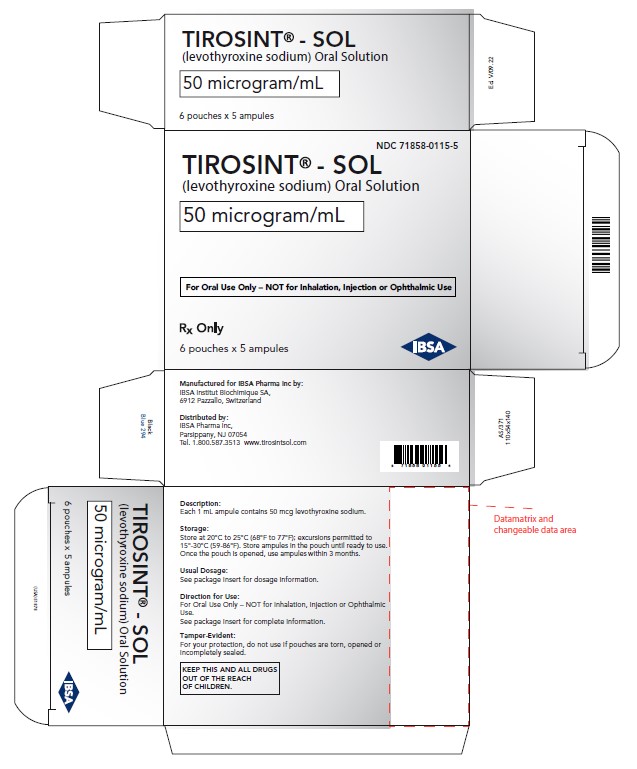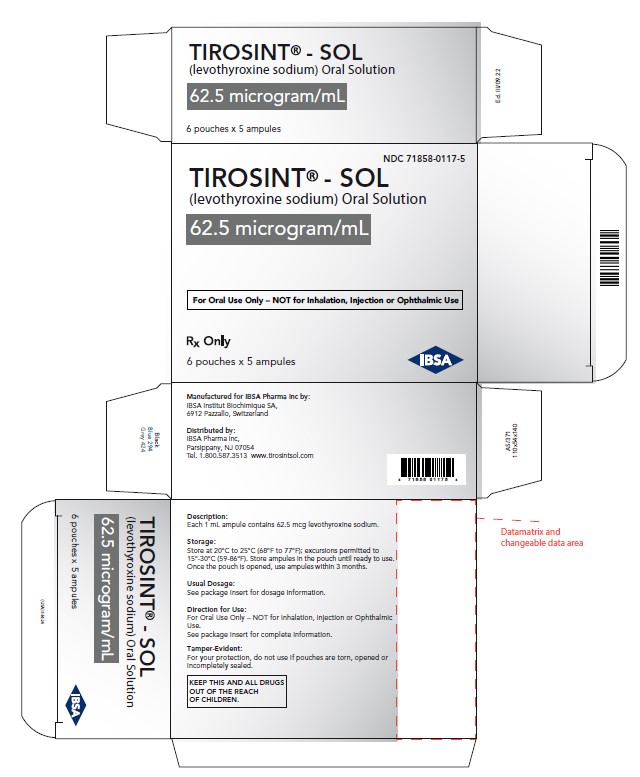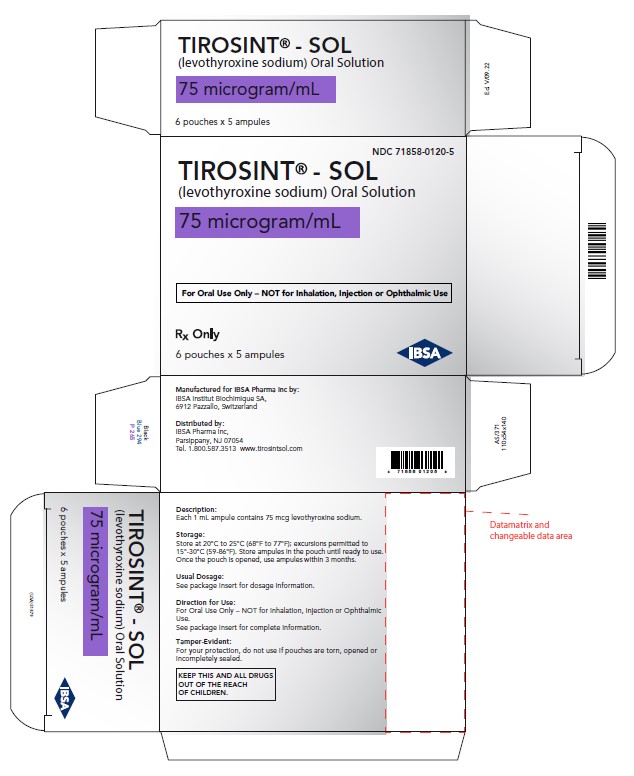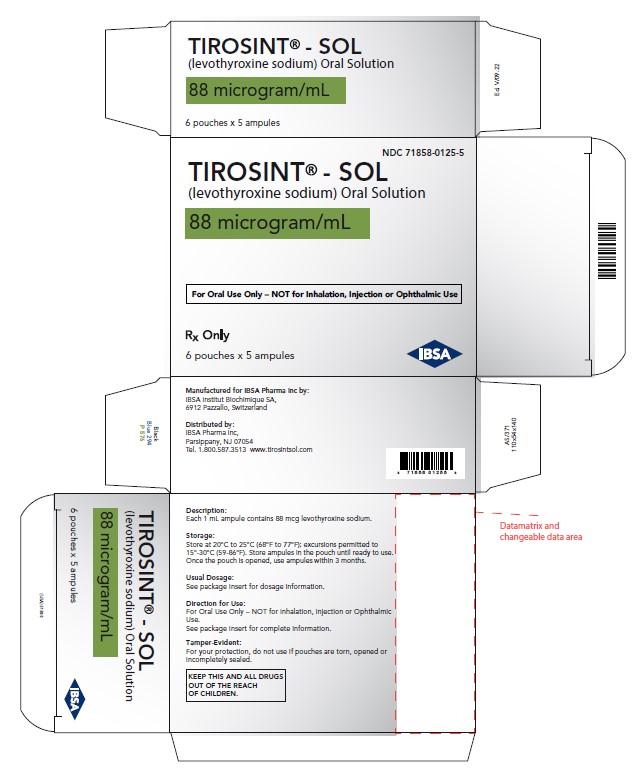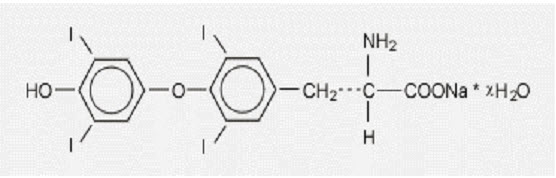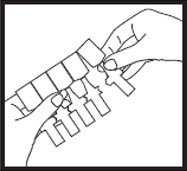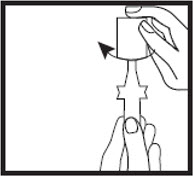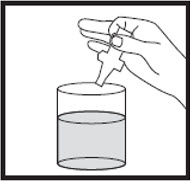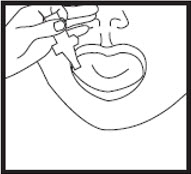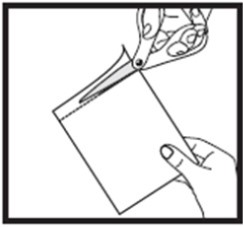 DRUG LABEL: Tirosint
NDC: 71858-0105 | Form: SOLUTION
Manufacturer: IBSA Pharma Inc.
Category: prescription | Type: HUMAN PRESCRIPTION DRUG LABEL
Date: 20250120

ACTIVE INGREDIENTS: LEVOTHYROXINE SODIUM 13 ug/1 mL
INACTIVE INGREDIENTS: WATER; GLYCERIN

HIGHLIGHTS OF PRESCRIBING INFORMATION

These highlights do not include all the information needed to use TIROSINT®-SOL safely and effectively. See full prescribing information for TIROSINT®-SOL.
Initial U.S. Approval: 2000

WARNING: NOT FOR TREATMENT OF OBESITY OR FOR WEIGHT LOSS

See full prescribing information for complete boxed warning

- Thyroid hormones, including TIROSINT-SOL, should not be used for the treatment of obesity or for weight loss.
- Doses beyond the range of daily hormonal requirements may produce serious or even life threatening manifestations of toxicity (6, 10).

RECENT MAJOR CHANGES

Indications and Usage (1) | 11/2023
Dosage and Administration (2.1) | 11/2023
Dosage and Administration (2.2) | 11/2023
Dosage and Administration (2.3) | 11/2023
Warnings and Precautions (5.1) | 11/2023
Warnings and Precautions (5.4) | 11/2023

1 INDICATION AND USAGE

TIROSINT-SOL is L-thyroxine (T4) indicated in adult and pediatric patients, including neonates, for:

- Hypothyroidism - As replacement therapy in primary (thyroidal), secondary (pituitary), and tertiary (hypothalamic) congenital or acquired hypothyroidism (1)
- Pituitary Thyrotropin (Thyroid-Stimulating Hormone, TSH) Suppression - As an adjunct to surgery and radioiodine therapy in the management of thyrotropin-dependent well-differentiated thyroid cancer (1)

Limitations of Use

- Not indicated for suppression of benign thyroid nodules and nontoxic diffuse goiter in iodine-sufficient patients (1)
- Not indicated for treatment of transient hypothyroidism during the recovery phase of subacute thyroiditis (1)

2 DOSAGE AND ADMINISTRATION

- Administer once daily, on an empty stomach, 15 minutes before breakfast (2.1)
- Administer at least 4 hours before or after drugs that are known to interfere with absorption (2.1)
- Evaluate the need for dose adjustments when regularly administering within an hour of certain foods that may affect TIROSINT-SOL absorption (2.1)
- To administer TIROSINT-SOL in water, squeeze the contents of one single unit-dose ampule into a glass or cup containing water (2.1)
- To administer TIROSINT-SOL directly, either squeeze it into the mouth OR onto a spoon and immediately consume (2.1)
- Starting dose depends on a variety of factors, including age, body weight, cardiovascular status, and concomitant medications, co-administered food, and the specific nature of the condition being treated. Peak therapeutic effect may not be attained for 4-6 weeks (2.2)
- See full prescribing information for dosing in specific patient populations (2.3)
- Adequacy of therapy determined with periodic monitoring of TSH and/or T4 as well as clinical status (2.4)

3 DOSAGE FORMS AND STRENGTHS

Oral solution: 13, 25, 37.5, 44, 50, 62.5, 75, 88, 100, 112, 125, 137, 150, 175, 200 mcg/mL (3)

4 CONTRAINDICATIONS

- Hypersensitivity to glycerol (4)
- Uncorrected adrenal insufficiency (4)

5 WARNINGS AND PRECAUTIONS

- Serious risks related to overtreatment or undertreatment with TIROSINT-SOL: Titrate the dose of TIROSINT-SOL carefully and monitor response to titration. (5.1)
- Cardiac adverse reactions in the elderly and in patients with underlying cardiovascular disease: Initiate TIROSINT-SOL at less than the full replacement dose because of the increased risk of cardiac adverse reactions, including atrial fibrillation. (2.3, 5.2, 8.5)
- Myxedema coma: Do not use oral thyroid hormone drug products to treat myxedema coma. (5.3)
- Acute adrenal crisis in patients with concomitant adrenal insufficiency: Treat with replacement glucocorticoids prior to initiation of TIROSINT‑SOL treatment. (5.4)
- Worsening of diabetic control: therapy in patients with diabetes mellitus may worsen glycemic control and result in increased antidiabetic agent or insulin requirements. Carefully monitor glycemic control after starting, changing, or discontinuing thyroid hormone therapy. (5.5)
- Decreased bone mineral density associated with thyroid hormone over-replacement: Over-replacement can increase bone resorption and decrease bone mineral density. Give the lowest effective dose. 5.6)

6 ADVERSE REACTIONS

Adverse reactions associated with TIROSINT-SOL are primarily those of hyperthyroidism due to therapeutic overdosage including: arrhythmias, myocardial infarction, dyspnea, muscle spasm, headache, nervousness, irritability, insomnia, tremors, muscle weakness, increased appetite, weight loss, diarrhea, heat intolerance, menstrual irregularities, and skin rash (6)

To report SUSPECTED ADVERSE REACTIONS, contact IBSA Pharma Inc. at 1-800-587-3513, or FDA at 1-800-FDA-1088 or www.fda.gov/medwatch.

7 DRUG INTERACTIONS

See full prescribing information for drugs that affect thyroid hormone pharmacokinetics and metabolism (e.g., absorption, synthesis, secretion, catabolism, protein binding, and target tissue response) and may alter the therapeutic response to TIROSINT-SOL (7)

8 USE IN SPECIFIC POPULATIONS

Pregnancy may require the use of higher doses of TIROSINT-SOL (2.3, 8.1)

See 17 for PATIENT COUNSELING INFORMATION and FDA‑approved patient labeling.

FULL PRESCRIBING INFORMATION

WARNING: NOT FOR TREATMENT OF OBESITY OR FOR WEIGHT LOSS

- Thyroid hormones, including TIROSINT-SOL, either alone or with other therapeutic agents, should not be used for the treatment of obesity or for weight loss.
- In euthyroid patients, doses within the range of daily hormonal requirements are ineffective for weight reduction.
- Larger doses may produce serious or even life threatening manifestations of toxicity, particularly when given in association with sympathomimetic amines such as those used for their anorectic effects [see Adverse Reactions (6), Drug Interactions (7.7), and Overdosage (10)].

1 INDICATION AND USAGE

Hypothyroidism

TIROSINT-SOL is indicated in adult and pediatric patients, including neonates, as a replacement therapy in primary (thyroidal), secondary (pituitary), and tertiary (hypothalamic) congenital or acquired hypothyroidism.

Pituitary Thyrotropin (Thyroid-Stimulating Hormone, TSH) Suppression

TIROSINT-SOL is indicated in adult and pediatric patients, including neonates, as an adjunct to surgery and radioiodine therapy in the management of thyrotropin-dependent well-differentiated thyroid cancer.

Limitations of Use

- Tirosint-SOL is not indicated for suppression of benign thyroid nodules and nontoxic diffuse goiter in iodine-sufficient patients as there are no clinical benefits and overtreatment with TIROSINT-SOL may induce hyperthyroidism [see Warnings and Precautions (5.1)] .
- Tirosint-SOL is not indicated for treatment of transient hypothyroidism during the recovery phase of subacute thyroiditis.

2 DOSAGE AND ADMINISTRATION

2.1 General Administration Information

Administer TIROSINT-SOL as a single daily oral dose, on an empty stomach,15 minutes before breakfast.

Administer TIROSINT-SOL at least 4 hours before or after drugs known to interfere with TIROSINT-SOL absorption [see Drug Interactions (7.1)] .

Evaluate the need for dose adjustments when regularly administering within an hour of certain foods that may affect TIROSINT-SOL absorption [see Dosage and Administration (2.2 and 2.3), Drug Interactions (7.9) and Clinical Pharmacology (12.3)] .

TIROSINT-SOL may be administered in water or directly into the mouth:

- To administer TIROSINT-SOL in water, squeeze the contents of one single unit-dose ampule into a glass or cup containing water. Stir the diluted TIROSINT-SOL and drink all of it immediately. Rinse the glass or cup with additional water and drink the contents to ensure that the total dose is taken. Do not dilute TIROSINT-SOL in a medium other than water. Open the ampule and prepare the solution immediately before intake.
- To administer TIROSINT-SOL directly (without water), either squeeze it into the mouth OR onto a spoon and immediately consume.

2.2 Important Considerations for Dosing

The dosage of TIROSINT-SOL for hypothyroidism or pituitary TSH suppression depends on a variety of factors including: the patient's age, body weight, cardiovascular status, concomitant medical conditions (including pregnancy), concomitant medications, co-administered food, and the specific nature of the condition being treated [see Dosage and Administration (2.3), Warnings and Precautions (5), and Drug Interactions (7)] . Dosing must be individualized to account for these factors and dosage adjustments made based on periodic assessment of the patient's clinical response and laboratory parameters [see Dosage and Administration (2.4)] .

For adult patients with primary hypothyroidism, titrate until the patient is clinically euthyroid and the serum TSH returns to normal [see Dosage and Administration (2.3)].

For secondary or tertiary hypothyroidism, serum TSH is not a reliable measure of TIROSINT-SOL dosage adequacy and should not be used to monitor therapy. Use the serum free-T4 level to titrate TIROSINT-SOL dosing until the patient is clinically euthyroid and the serum free-T4 level is restored to the upper half of the normal range [see Dosage and Administration (2.3)].

The peak therapeutic effect of a given dose of TIROSINT-SOL may not be attained for 4 to 6 weeks.

2.3 Recommended Dosage and Titration

Primary, Secondary, and Tertiary Hypothyroidism in Adults

The recommended starting daily dosage of TIROSINT-SOL in adults with primary, secondary, or tertiary hypothyroidism is based on age and comorbid cardiac conditions, as described in Table 1. For patients at risk of atrial fibrillation or patients with underlying cardiac disease, start with a lower dosage and titrate the dosage more slowly to avoid exacerbation of cardiac symptoms. Dosage titration is based on serum TSH or free-T4 [see Dosage and Administration (2.2)].

Table 1. TIROSINT-SOL Dosing Guidelines for Hypothyroidism in Adults*

Patient Population | Starting Dosage | Dosage Titration Based on; Serum TSH or Free-T4
Adults diagnosed with hypothyroidism | Full replacement dose is 1.6 mcg/kg/day. Some patients require a lower starting dose. | Titrate dosage by 12.5 to 25 mcg increments every 4 to 6 weeks, as needed until the patient is euthyroid.
Adults at risk for atrial fibrillation or with underlying cardiac disease | Lower starting dose (less than 1.6 mcg/kg/day) | Titrate dosage every 6 to 8 weeks, as needed until the patient is euthyroid.
Geriatric patients | Lower starting dose (less than 1.6 mcg/kg/day) | Titrate dosage every 6 to 8 weeks, as needed until the patient is euthyroid.

*Dosages greater than 200 mcg/day are seldom required. An inadequate response to daily dosages greater than 300 mcg/day is rare and may indicate poor compliance, malabsorption, drug interactions, or a combination of these factors [see Dosage and Administration (2.1) and Drug Interactions (7)].

Primary, Secondary, and Tertiary Hypothyroidism in Pediatric Patients

The recommended starting daily dosage of TIROSINT-SOL in pediatric patients with primary, secondary, or tertiary hypothyroidism is based on body weight and changes with age as described in Table 2. Titrate the dosage (every 2 weeks) as needed based on serum TSH or free-T4 until the patient is euthyroid [see Dosage and Administration (2.2)].

Table 2. TIROSINT-SOL Dosing Guidelines for Hypothyroidism in Pediatric Patients

Age | Starting Daily Dosage Per Kg Body Weight*
0-3 months | 10-15 mcg/kg/day
3-6 months | 8-10 mcg/kg/day
6-12 months | 6-8 mcg/kg/day
1-5 years | 5-6 mcg/kg/day
6-12 years | 4-5 mcg/kg/day
Greater than 12 years but growth and puberty incomplete | 2-3 mcg/kg/day
Growth and puberty complete | 1.6 mcg/kg/day

*Adjust dosage based on clinical response and laboratory parameters [see Dosage and Administration (2.4) and Use in Specific Populations (8.4)].

Pediatric Patients from Birth to 3 Months of Age at Risk for Cardiac Failure

Start at a lower starting dosage and increase the dosage every 4 to 6 weeks as needed based on clinical and laboratory response.

Pediatric Patients at Risk for Hyperactivity

To minimize the risk of hyperactivity, start at one-fourth the recommended full replacement dosage, and increase on a weekly basis by one-fourth the full recommended replacement dosage until the full recommended replacement dosage is reached.

Hypothyroidism in Pregnant Patients

For pregnant patients with pre-existing hypothyroidism, measure serum TSH and free-T4 as soon as pregnancy is confirmed and, at minimum, during each trimester of pregnancy. In pregnant patients with primary hypothyroidism, maintain serum TSH in the trimester-specific reference range.

The recommended daily dosage of TIROSINT-SOL in pregnant patients is described in Table 3.

Table 3. TIROSINT-SOL Dosing Guidelines for Hypothyroidism in Pregnant Patients

Patient Population | Starting Dosage | Dose Adjustment and Titration
Pre-existing primary hypothyroidism with serum TSH above normal trimester-specific range | Pre-pregnancy dosage may increase during pregnancy | Increase TIROSINT-SOL dosage by 12.5 to 25 mcg per day. Monitor TSH every 4 weeks until a stable dose is reached and serum TSH is within normal trimester-specific range.; Reduce TIROSINT-SOL dosage to pre-pregnancy levels immediately after delivery. Monitor serum TSH 4 to 8 weeks postpartum.
New onset hypothyroidism TSH > 10 mIU per liter) | 1.6 mcg/kg/day | Monitor serum TSH every 4 weeks and adjust TIROSINT-SOL dosage until serum TSH is within normal trimester-specific range.
New onset hypothyroidism (TSH < 10 mIU per liter) | 1.0 mcg/kg/day | Monitor serum TSH every 4 weeks and adjust TIROSINT-SOL dosage until serum TSH is within normal trimester-specific range.

TSH Suppression in Well-differentiated Thyroid Cancer in Adults and Pediatric Patients

The TIROSINT-SOL dosage is based on the target level of TSH suppression for the stage and clinical status of thyroid cancer.

2.4 Monitoring TSH and/or Thyroxine (T4) Levels

Assess the adequacy of therapy by periodic assessment of laboratory tests and clinical evaluation. Persistent clinical and laboratory evidence of hypothyroidism, despite an apparent adequate replacement dose of TIROSINT-SOL, may be evidence of inadequate absorption, poor compliance, drug interactions, or a combination of these factors.

Adults

In adult patients with primary hypothyroidism, monitor serum TSH levels after an interval of 6 to 8 weeks after any change in dosage. In patients on a stable and appropriate replacement dosage, evaluate clinical and biochemical response every 6 to 12 months and whenever there is a change in the patient's clinical status.

Pediatrics Patients

In patients with hypothyroidism, assess the adequacy of replacement therapy by measuring both serum TSH and total or free-T4. Monitor TSH and total or free-T4 in pediatric patients as follows: 2 and 4 weeks after the initiation of treatment, 2 weeks after any change in dosage, and then every 3 to 12 months thereafter following dosage stabilization until growth is completed. Poor compliance or abnormal values may necessitate more frequent monitoring. Perform routine clinical examination, including assessment of mental and physical growth and development, and bone maturation, at regular intervals.

The general aim of therapy is to normalize the serum TSH level. TSH may not normalize in some patients due to in utero hypothyroidism causing a resetting of pituitary-thyroid feedback. Failure of the serum T4 to increase into the upper half of the normal range within 2 weeks of initiation of TIROSINT-SOL therapy and/or of the serum TSH to decrease below 20 mIU per Liter within 4 weeks may indicate the patient is not receiving adequate therapy. Assess compliance, dose of medication administered, and method of administration prior to increasing the dose of TIROSINT-SOL [see Warning and Precautions (5.1) and Use in Specific Populations (8.4)] .

Secondary (Pituitary) and Tertiary (Hypothalamic) Hypothyroidism

Monitor serum free-T4 levels and maintain in the upper half of the normal range in these patients.

3 DOSAGE FORMS AND STRENGTHS

TIROSINT-SOL oral solution is a clear, colorless to slightly yellow solution supplied in a 1 mL white, non-transparent, unit-dose ampule. Each ampule bears a colored label with the dosage strength and the product name (TIROSINT-SOL) (Table 4).

Table 4. TIROSINT-SOL Solution Strengths and Identifying Features

Strength (mcg/mL) | Color
13 | Green
25 | Orange
37.5 | Dark Blue
44 | Red
50 | White
75 | Purple
62.5 | Grey
88 | Olive
100 | Yellow
112 | Rose
125 | Brown
137 | Turquoise
150 | Blue
175 | Lilac
200 | Pink

4 CONTRAINDICATIONS

TIROSINT-SOL is contraindicated in patients with:

- Hypersensitivity to glycerol, the inactive ingredient in TIROSINT-SOL [see Adverse Events (6)].
- Uncorrected adrenal insufficiency [see Warnings and Precautions (5.4)]

5 WARNINGS AND PRECAUTIONS

5.1 Serious Risks Related to Overtreatment or Undertreatment with TIROSINT-SOL

TIROSINT-SOL has a narrow therapeutic index. Overtreatment or undertreatment with TIROSINT-SOL may have negative effects on growth and development, cardiovascular function, bone metabolism, reproductive function, cognitive function, gastrointestinal function, and glucose and lipid metabolism in adult or pediatric patients.

In pediatric patients with congenital and acquired hypothyroidism, undertreatment may adversely affect cognitive development and linear growth, and overtreatment is associated with craniosynostosis and acceleration of bone age [see Use in Specific Populations (8.4)].

Titrate the dose of TIROSINT-SOL carefully and monitor response to titration to avoid these effects [see Dosage and Administration (2.4)]. Consider the potential for food or drug interactions and adjust the administration or dosage of TIROSINT-SOL as needed [see Dosage and Administration (2.4), Drug Interactions (7.1), and Clinical Pharmacology (12.3)].

5.2 Cardiac Adverse Reactions in the Elderly and in Patients with Underlying Cardiovascular Disease

Overtreatment with levothyroxine may cause an increase in heart rate, cardiac wall thickness, and cardiac contractility, and may precipitate angina or arrhythmias, particularly in patients with cardiovascular disease and in elderly patients. Initiate TIROSINT-SOL therapy in this population at lower doses than those recommended in younger individuals or in patients without cardiac disease [see Dosage and Administration (2.3) and Use in Specific Populations (8.5)].

Monitor for cardiac arrhythmias during surgical procedures in patients with coronary artery disease receiving suppressive TIROSINT-SOL therapy. Monitor patients receiving concomitant TIROSINT-SOL and sympathomimetic agents for signs and symptoms of coronary insufficiency . If cardiac symptoms develop or worsen, reduce the TIROSINT-SOL dose or withhold it for one week and restart at a lower dose.

5.3 Myxedema Coma

Myxedema coma is a life-threatening emergency characterized by poor circulation and hypometabolism, and may result in unpredictable absorption of levothyroxine sodium from the gastrointestinal tract. Use of oral thyroid hormone drug products is not recommended to treat myxedema coma. Administer thyroid hormone products formulated for intravenous administration to treat myxedema coma.

5.4 Acute Adrenal Crisis in Patients with Concomitant Adrenal Insufficiency

Thyroid hormone increases metabolic clearance of glucocorticoids. Initiation of thyroid hormone therapy prior to initiating glucocorticoid therapy may precipitate an acute adrenal crisis in patients with adrenal insufficiency. Treat patients with adrenal insufficiency with replacement glucocorticoids prior to initiating treatment with TIROSINT-SOL [see Contraindications (4)].

5.5 Worsening of Diabetic Control

Addition of levothyroxine therapy in patients with diabetes mellitus may worsen glycemic control and result in increased antidiabetic agent or insulin requirements. Carefully monitor glycemic control after starting, changing, or discontinuing TIROSINT-SOL [see Drug Interactions (7.2)] .

5.6 Decreased Bone Mineral Density Associated with Thyroid Hormone Over-Replacement

Increased bone resorption and decreased bone mineral density may occur as a result of levothyroxine over-replacement, particularly in post-menopausal women. The increased bone resorption may be associated with increased serum levels and urinary excretion of calcium and phosphorous, elevations in bone alkaline phosphatase, and suppressed serum parathyroid hormone levels. Administer the minimum dose of TIROSINT-SOL that achieves the desired clinical and biochemical response to mitigate this risk.

6 ADVERSE REACTIONS

Adverse reactions associated with TIROSINT-SOL therapy are primarily those of hyperthyroidism due to therapeutic overdosage [see Warnings and Precautions (5) and Overdosage (10)]. They include the following:

- General: fatigue, increased appetite, weight loss, heat intolerance, fever, excessive sweating
- Central nervous system: headache, hyperactivity, nervousness, anxiety, irritability, emotional lability, insomnia
- Musculoskeletal: tremors, muscle weakness, muscle spasm
- Cardiovascular: palpitations, tachycardia, arrhythmias, increased pulse and blood pressure, heart failure, angina, myocardial infarction, cardiac arrest
- Respiratory: dyspnea
- Gastrointestinal (GI): diarrhea, vomiting, abdominal cramps, elevations in liver function tests
- Dermatologic: hair loss, flushing, rash
- Endocrine: decreased bone mineral density
- Reproductive: menstrual irregularities, impaired fertility

Seizures have been reported rarely with the institution of levothyroxine therapy.

Adverse Reactions in Pediatric Patients

Pseudotumor cerebri and slipped capital femoral epiphysis have been reported in pediatric patients receiving levothyroxine therapy. Overtreatment may result in craniosynostosis in infants who have not undergone closure of the fontanelles, and in premature closure of the epiphyses in pediatric patients still experiencing growth with resultant compromised adult height.

Hypersensitivity Reactions

Hypersensitivity reactions to inactive ingredients have occurred in patients treated with thyroid hormone products. These include urticaria, pruritus, skin rash, flushing, angioedema, various GI symptoms (abdominal pain, nausea, vomiting and diarrhea), fever, arthralgia, serum sickness, and wheezing. Hypersensitivity to levothyroxine itself is not known to occur.

7 DRUG INTERACTIONS

7.1 Drugs Known to Affect Thyroid Hormone Pharmacokinetics

Many drugs can exert effects on thyroid hormone pharmacokinetics and metabolism (e.g., absorption, synthesis, secretion, catabolism, protein binding, and target tissue response) and may alter the therapeutic response to TIROSINT-SOL (Tables 5 to 8).

Table 5. Drugs That May Decrease T4 Absorption (Hypothyroidism)

Potential impact: Concurrent use may reduce the efficacy of TIROSINT-SOL by binding and delaying or preventing absorption, potentially resulting in hypothyroidism.
Drug or Drug Class | Effect
Phosphate Binders (e.g., calcium carbonate, ferrous sulfate, sevelamer, lanthanum) | Phosphate binders may bind to levothyroxine. Administer TIROSINT-SOL at least 4 hours apart from these agents.
Orlistat | Monitor patients treated concomitantly with orlistat and TIROSINT‑SOL for changes in thyroid function.
Bile Acid Sequestrants; (e.g., colesevelam, cholestyramine, colestipol; Ion Exchange Resins; (e.g., Kayexalate) | Bile acid sequestrants and ion exchange resins are known to decrease levothyroxine absorption. Administer TIROSINT-SOL at least 4 hours prior to these drugs or monitor TSH levels.
Sucralfate; Antacids; (e.g., aluminum & magnesium hydroxides, simethicone) | Gastric acidity is an essential requirement for adequate absorption of levothyroxine. However, gastric acidity may not be as essential for the absorption of TIROSINT-SOL. Sucralfate and antacids may cause hypochlorhydria, affect gastric pH, and reduce levothyroxine absorption. Monitor patients appropriately.

Table 6. Drugs That May Alter T4 and Triiodothyronine (T3) Serum Transport Without Affecting Free Thyroxine (FT4) Concentration (Euthyroidism)

Drug or Drug Class | Effect
Clofibrate; Estrogen-containing oral contraceptives; Estrogens (oral); Heroin / Methadone; 5-Fluorouracil; Mitotane; Tamoxifen | These drugs may increase serum thyroxine-binding globulin (TBG) concentration.
Androgens / Anabolic Steroids Asparaginase Glucocorticoids Slow-Release Nicotinic Acid | These drugs may decrease serum TBG concentration.
Potential impact (below): Administration of these agents with TIROSINT-SOL results in an initial transient increase in FT4. Continued administration results in a decrease in serum T4 and normal FT4 and TSH concentrations.
Salicylates (> 2 g/day) | Salicylates inhibit binding of T4 and T3 to TBG and transthyretin. An initial increase in serum FT4 is followed by return of FT4 to normal levels with sustained therapeutic serum salicylate concentrations, although total T4 levels may decrease by as much as 30%.
Other drugs:; Carbamazepine; Furosemide (> 80 mg IV); Heparin; Hydantoins; Non-Steroidal Anti-inflammatory Drugs:; Fenamates | These drugs may cause protein-binding site displacement. Furosemide has been shown to inhibit the protein binding of T4 to TBG and albumin, causing an increase free‑T4 fraction in serum. Furosemide competes for T4-binding sites on TBG, prealbumin, and albumin, so that a single high dose can acutely lower the total T4 level. Phenytoin and carbamazepine reduce serum protein binding of levothyroxine, and total and free‑T4 may be reduced by 20% to 40%, but most patients have normal serum TSH levels and are clinically euthyroid. Closely monitor thyroid hormone parameters.

Table 7. Drugs That May Alter Hepatic Metabolism of T4 (Hypothyroidism)

Potential impact: Stimulation of hepatic microsomal drug-metabolizing enzyme activity may cause increased hepatic degradation of levothyroxine, resulting in increased TIROSINT-SOL requirements.
Drug or Drug Class | Effect
Phenobarbital; Rifampin | Phenobarbital has been shown to reduce the response to thyroxine. Phenobarbital increases L-thyroxine metabolism by inducing uridine 5’ diphospho-glucuronosyltransferase (UGT) and leads to a lower T4 serum levels. Changes in thyroid status may occur if barbiturates are added or withdrawn from patients being treated for hypothyroidism. Rifampin has been shown to accelerate the metabolism of levothyroxine.

Table 8. Drugs That May Decrease Conversion of T4 to T3

Potential impact: Administration of these enzyme inhibitors decreases the peripheral conversion of T4 to T3, leading to decreased T3 levels. However, serum T4 levels are usually normal but may occasionally be slightly increased.
Drug or Drug Class | Effect
Beta-adrenergic antagonists; (e.g., Propranolol > 160 mg/day) | In patients treated with large doses of propranolol (> 160 mg/day), T3 and T4 levels change, TSH levels remain normal, and patients are clinically euthyroid. Actions of particular beta-adrenergic antagonists may be impaired when a hypothyroid patient is converted to the euthyroid state.
Glucocorticoids; (e.g., Dexamethasone > 4 mg/day) | Short-term administration of large doses of glucocorticoids may decrease serum T3 concentrations by 30% with minimal change in serum T4 levels. However, long-term glucocorticoid therapy may result in slightly decreased T3 and T4 levels due to decreased TBG production (See above).
Other drugs:; Amiodarone | Amiodarone inhibits peripheral conversion of T4 to T3 and may cause isolated biochemical changes (increase in serum free-T4, and decrease or normal free-T3) in clinically euthyroid patients.

7.2 Antidiabetic Therapy

Addition of TIROSINT-SOL therapy in patients with diabetes mellitus may worsen glycemic control and result in increased antidiabetic agent or insulin requirements. Carefully monitor glycemic control, especially when thyroid therapy is started, changed, or discontinued [see Warnings and Precautions (5.5)] .

7.3 Oral Anticoagulants

TIROSINT-SOL increases the response to oral anticoagulant therapy. Therefore, a decrease in the dose of anticoagulant may be warranted with correction of the hypothyroid state or when the TIROSINT-SOL dose is increased. Closely monitor coagulation tests to permit appropriate and timely dosage adjustments.

7.4 Digitalis Glycosides

TIROSINT-SOL may reduce the therapeutic effects of digitalis glycosides. Serum digitalis glycoside levels may decrease when a hypothyroid patient becomes euthyroid, necessitating an increase in the dose of digitalis glycosides.

7.5 Antidepressant Therapy

Concurrent use of tricyclic (e.g., amitriptyline) or tetracyclic (e.g., maprotiline) antidepressants and TIROSINT-SOL may increase the therapeutic and toxic effects of both drugs, possibly due to increased receptor sensitivity to catecholamines. Toxic effects may include increased risk of cardiac arrhythmias and central nervous system stimulation. TIROSINT-SOL may accelerate the onset of action of tricyclics. Administration of sertraline in patients stabilized on TIROSINT-SOL may result in increased TIROSINT-SOL requirements.

7.6 Ketamine

Concurrent use of ketamine and TIROSINT-SOL may produce marked hypertension and tachycardia. Closely monitor blood pressure and heart rate in these patients.

7.7 Sympathomimetics

Concurrent use of sympathomimetics and TIROSINT-SOL may increase the effects of sympathomimetics or thyroid hormone. Thyroid hormones may increase the risk of coronary insufficiency when sympathomimetic agents are administered to patients with coronary artery disease.

7.8 Tyrosine-Kinase Inhibitors

Concurrent use of tyrosine-kinase inhibitors such as imatinib may cause hypothyroidism. Closely monitor TSH levels in such patients.

7.9 Drug-Food Interactions

Consumption of certain foods may affect TIROSINT-SOL absorption thereby necessitating adjustments in dosing [see Dosage and Administration (2.1)] . Soybean flour (infant formula), cottonseed meal, walnuts, and dietary fiber may bind and decrease the absorption of TIROSINT-SOL from the gastrointestinal tract. Grapefruit juice may delay the absorption of levothyroxine and reduce its bioavailability.

7.10 Drug-Laboratory Test Interactions

Consider changes in TBG concentration when interpreting T4 and T3 values. Measure and evaluate unbound (free) hormone and/or determine the free-T4 index (FT4I) in this circumstance. Pregnancy, infectious hepatitis, estrogens, estrogen-containing oral contraceptives, and acute intermittent porphyria increase TBG concentrations. Nephrosis, severe hypoproteinemia, severe liver disease, acromegaly, androgens and corticosteroids decrease TBG concentration. Familial hyper- or hypo-thyroxine binding globulinemias have been described, with the incidence of TBG deficiency approximating 1 in 9000.

8 USE IN SPECIFIC POPULATIONS

8.1 Pregnancy

Risk Summary

The clinical experience, including data from published postmarketing studies, in pregnant women treated with oral levothyroxine to maintain euthyroid state have not reported increased rates of major birth defects, miscarriages, or other adverse maternal or fetal outcomes. There are risks to the mother and fetus associated with untreated hypothyroidism in pregnancy. Since TSH levels may increase during pregnancy, TSH should be monitored and TIROSINT‑SOL dosage adjusted during pregnancy [see Clinical Considerations] . Animal reproductive studies have not been conducted with levothyroxine sodium. TIROSINT-SOL should not be discontinued during pregnancy and hypothyroidism diagnosed during pregnancy should be promptly treated.

The estimated background risk of major birth defects and miscarriage for the indicated population is unknown. All pregnancies have a background risk of birth defect, loss, or other adverse outcomes. In the U.S. general population, the estimated background risk of major birth defects and miscarriage in clinically recognized pregnancies is 2% to 4% and 15% to 20%, respectively.

Clinical Considerations

Disease-Associated Maternal and/or Embryo/Fetal Risk

Maternal hypothyroidism during pregnancy is associated with a higher rate of complications, including spontaneous abortion, gestational hypertension, pre-eclampsia, stillbirth, and premature delivery. Untreated maternal hypothyroidism may have an adverse effect on fetal neurocognitive development.

Dose Adjustments During Pregnancy and the Postpartum Period

Pregnancy may increase TIROSINT-SOL requirements. Serum TSH levels should be monitored and the TIROSINT-SOL dosage adjusted during pregnancy. Since postpartum TSH levels are similar to preconception values, the TIROSINT-SOL dosage should return to the pre-pregnancy dose immediately after delivery [see Dosage and Administration (2.3)].

8.2 Lactation

Risk Summary

Published studies report that levothyroxine is present in human milk following the administration of oral levothyroxine. No adverse effects on the breastfed infant have been reported and this no information on the effects of levothyroxine on milk production. Adequate levothyroxine treatment during lactation may normalize milk production in hypothyroid lactating mothers with low milk supply. The developmental and health benefits of breastfeeding should be considered along with the mother’s clinical need for TIROSINT-SOL and any potential adverse effects on the breastfed infant from TIROSINT-SOL or from the underlying maternal condition.

8.4 Pediatric Use

TIROSINT-SOL is indicated in patients from birth to less than 17 years of age:

- As a replacement therapy in primary (thyroidal), secondary (pituitary), and tertiary (hypothalamic) congenital or acquired hypothyroidism
- As an adjunct to surgery and radioiodine therapy in the management of thyrotropin-dependent well-differentiated thyroid cancer

Rapid restoration of normal serum T4 concentrations is essential for preventing the adverse effects of congenital hypothyroidism on cognitive development as well as on overall physical growth and maturation. Therefore, initiate TIROSINT-SOL therapy immediately upon diagnosis. Levothyroxine is generally continued for life in these patients [see Warnings and Precautions (5.1)].

Closely monitor infants during the first two weeks of TIROSINT-SOL therapy for cardiac overload and arrhythmias.

8.5 Geriatric Use

Because of the increased prevalence of cardiovascular disease among the elderly, initiate TIROSINT-SOL at less than the full replacement dose [ see Dosage and Administration (2.3) and Warnings and Precautions (5.1)]. Atrial arrhythmias can occur in elderly patients. Atrial fibrillation is the most common of the arrhythmias observed with levothyroxine overtreatment in the elderly .

10 OVERDOSAGE

The signs and symptoms of overdosage are those of hyperthyroidism [see Warnings and Precautions (5) and Adverse Reactions (6)]. In addition, confusion and disorientation may occur. Cerebral embolism, shock, coma, and death have been reported. Seizures occurred in a 3-year-old child ingesting 3.6 mg of levothyroxine. Symptoms may not necessarily be evident or may not appear until several days after ingestion of levothyroxine sodium.

Reduce the TIROSINT-SOL dose or discontinue temporarily if signs or symptoms of overdosage occur. Initiate appropriate supportive treatment as dictated by the patient's medical status.

For current information on the management of poisoning or overdosage, contact the National Poison Control Center at 1-800-222-1222 or www.poison.org.

11 DESCRIPTION

TIROSINT-SOL (levothyroxine sodium) oral solution contains synthetic L-3,3',5,5'-tetraiodothyronine sodium salt [levothyroxine (T4) sodium]. Synthetic T4 is chemically identical to that produced in the human thyroid gland. Levothyroxine (T4) sodium has an empirical formula of C15H10I4NNaO4 ∙ x H2O (where x = 5), molecular weight of 798.86 g/mol (anhydrous), and structural formula as shown:

TIROSINT-SOL oral solution is a clear, colorless to slightly yellow solution supplied in a 1 mL white, non-transparent, unit-dose ampule and is available in the following strengths (mcg/mL): 13, 25, 37.5, 44, 50, 62.5, 75, 88, 100, 112, 125, 137, 150, 175, 200.

The inactive ingredients in TIROSINT-SOL are glycerol and water.

12 CLINICAL PHARMACOLOGY

12.1 Mechanism of Action

Thyroid hormones exert their physiologic actions through control of DNA transcription and protein synthesis. Triiodothyronine (T3) and L-thyroxine (T4) diffuse into the cell nucleus and bind to thyroid receptor proteins attached to DNA. This hormone nuclear receptor complex activates gene transcription and synthesis of messenger RNA and cytoplasmic proteins.

The physiological actions of thyroid hormones are produced predominantly by T3, the majority of which (approximately 80%) is derived from T4 by deiodination in peripheral tissues.

12.2 Pharmacodynamics

Oral levothyroxine sodium is a synthetic T4 hormone that exerts the same physiologic effect as endogenous T4, thereby maintaining normal T4 levels when a deficiency is present.

12.3 Pharmacokinetics

Absorption

Absorption of orally administered T4 from the gastrointestinal (GI) tract ranges from 40% to 80%. The majority of the levothyroxine dose is absorbed from the jejunum and upper ileum. The relative bioavailability of TIROSINT-SOL compared to TIROSINT capsules, is approximately 98%. T4 absorption is increased by fasting, and decreased in malabsorption syndromes and by certain foods such as soybeans. Dietary fiber decreases the bioavailability of T4. Absorption may also decrease with age. In addition, many drugs and foods affect T4 absorption [see Drug Interactions (7)].

Effect of Food

No clinically significant differences in levothyroxine pharmacokinetics were observed between Tirosint-SOL administered 15 minutes and 30 minutes before a high-fat high-calorie meal (about 800 – 1000 kcal, 50% fat) [see Dosage and Administration (2.1)].

Distribution

Circulating thyroid hormones are greater than 99% bound to plasma proteins, including thyroxine-binding globulin (TBG), thyroxine-binding prealbumin (TBPA), and thyroxine-binding albumin (TBA), whose capacities and affinities vary for each hormone. The higher affinity of both TBG and TBPA for T4 partially explains the higher serum levels, slower metabolic clearance, and longer half-life of T4 compared to T3. Protein-bound thyroid hormones exist in reverse equilibrium with small amounts of free hormone. Only unbound hormone is metabolically active. Many drugs and physiologic conditions affect the binding of thyroid hormones to serum proteins [see Drug Interactions (7)]. Thyroid hormones do not readily cross the placental barrier [see Use in Specific Populations (8.1)].

Elimination

Metabolism

T4 is slowly eliminated (Table 9) . The major pathway of thyroid hormone metabolism is through sequential deiodination. Approximately 80% of circulating T3 is derived from peripheral T4 by monodeiodination. The liver is the major site of degradation for both T4 and T3, with T4 deiodination also occurring at a number of additional sites, including the kidney and other tissues. Approximately 80% of the daily dose of T4 is deiodinated to yield equal amounts of T3 and reverse T3 (rT3). T3 and rT3 are further deiodinated to diiodothyronine. Thyroid hormones are also metabolized via conjugation with glucuronides and sulfates and excreted directly into the bile and gut where they undergo enterohepatic recirculation.

Excretion

Thyroid hormones are primarily eliminated by the kidneys. A portion of the conjugated hormone reaches the colon unchanged and is eliminated in the feces. Approximately 20% of T4 is eliminated in the stool. Urinary excretion of T4 decreases with age.

Table 9. Pharmacokinetic Parameters of Thyroid Hormones in Euthyroid Patients
Hormone | Ratio in Thyroglobulin | Biologic Potency | Half-Life (Days) | Protein Binding (%)*
Levothyroxine (T4) | 10 – 20 | 1 | 6 – 7** | 99.96
Liothyronine (T3) | 1 | 4 | ≤ 2 | 99.5

Drug Interaction Study

No clinically significant differences in TIROSINT-SOL pharmacokinetics were observed when orally coadministered with omeprazole.

13 NONCLINICAL TOXICOLOGY

13.1 Carcinogenesis, Mutagenesis, Impairment of Fertility

Long-term carcinogenicity studies in animals to evaluate the carcinogenic potential of levothyroxine have not been performed. Studies to evaluate mutagenic potential and animal fertility have not been performed.

16 HOW SUPPLIED/STORAGE AND HANDLING

How Supplied

TIROSINT-SOL (levothyroxine sodium) oral solution is a clear, colorless to slightly yellow solution supplied in a 1 mL white, non-transparent, unit-dose ampule. The dosage strength is identified on the box and the pouch, and is associated with a distinct color. Each ampule bears a colored label with the dosage strength and the product name (TIROSINT-SOL) (Table 10).

Table 10. TIROSINT-SOL Solution Strengths and Packaging Description
Strength (mcg/mL) | Colora | Box NDC (30 Unit-Dose Ampules) | Pouch NDC (5 Unit-Dose Ampules)
13 | Green | 71858-0105-5 | 71858-0105-4
25 | Orange | 71858-0110-5 | 71858-0110-4
37.5 | Dark Blue | 71858-0112-5 | 71858-0112-4
44 | Red | 71858-0113-5 | 71858-0113-4
50 | White | 71858-0115-5 | 71858-0115-4
62.5 | Grey | 71858-0117-5 | 71858-0117-4
75 | Purple | 71858-0120-5 | 71858-0120-4
88 | Olive | 71858-0125-5 | 71858-0125-4
100 | Yellow | 71858-0130-5 | 71858-0130-4
112 | Rose | 71858-0135-5 | 71858-0135-4
125 | Brown | 71858-0140-5 | 71858-0140-4
137 | Turquoise | 71858-0145-5 | 71858-0145-4
150 | Blue | 71858-0150-5 | 71858-0150-4
175 | Lilac | 71858-0155-5 | 71858-0155-4
200 | Pink | 71858-0160-5 | 71858-0160-4

Storage and Handling

Store TIROSINT-SOL in the original container (closed pouch) at 20°C to 25°C (68°F to 77°F); excursions permitted to 15° to 30°C (59°F to 86°F) [See USP Controlled Room Temperature].

Use TIROSINT-SOL oral solution within three (3) months after opening the pouch. Keep the ampules in the pouch until ready to use as important information may be lost (i.e., manufacturer/distributor names and distributor contact phone number).

17 PATIENT COUNSELING INFORMATION

Advise the patient and/or caregiver to read the FDA-approved patient labeling (Patient Information and Instructions for Use).

Dosing and Administration

- Instruct patients to take TIROSINT-SOL only as directed by their healthcare provider.
- Instruct patients to take TIROSINT-SOL 15 minutes before breakfast.
- Instruct patients about the TIROSINT-SOL dosing instructions.
- Inform patients that agents such as iron and calcium supplements and antacids can decrease the absorption of levothyroxine. Instruct patients not to take TIROSINT-SOL within 4 hours of these agents.
- Instruct patients to notify their healthcare provider should they become pregnant or are thinking of becoming pregnant while taking TIROSINT-SOL.

Important Information

- Inform patients that it may take several weeks before they notice an improvement in symptoms.
- Inform patients that the levothyroxine in TIROSINT-SOL is intended to replace a hormone that is normally produced by the thyroid gland. Generally, replacement therapy is to be taken for life.
- Inform patients that TIROSINT-SOL should not be used as a primary or adjunctive therapy in a weight control program.
- Instruct patients to notify their healthcare provider if they are taking any other medications, including prescription and over-the-counter preparations.
- Instruct patients to notify their healthcare provider of any other medical conditions, particularly heart disease, diabetes, clotting disorders, and adrenal or pituitary gland problems, as the dose of medications used to control these other conditions may need to be adjusted while taking TIROSINT-SOL. If they have diabetes, instruct patients to monitor their blood and/or urinary glucose levels as directed by their physician and immediately report any changes to their physician. If patients are taking anticoagulants, their clotting status should be checked frequently.
- Instruct patients to notify their physician or dentist that they are taking TIROSINT-SOL prior to any surgery.

Adverse Reactions

- Instruct patients to notify their healthcare provider if they experience any of the following symptoms: rapid or irregular heartbeat, chest pain, shortness of breath, leg cramps, headache, nervousness, irritability, sleeplessness, tremors, change in appetite, weight loss, vomiting, diarrhea, excessive sweating, heat intolerance, fever, changes in menstrual periods, hives or skin rash, or any other unusual medical event.
- Inform patients that partial hair loss may occur rarely during the first few months of TIROSINT-SOL therapy, but this is usually temporary.

Manufactured for IBSA Pharma Inc. by:

IBSA Institut Biochimique SA
6912 Pazzallo
Switzerland

Distributed by:

IBSA Pharma Inc.
Parsippany, NJ 07054
USA

PATIENT INFORMATION

TIROSINT®-SOL [tee-row-sent-sōl]
(levothyroxine sodium)
oral solution

What is the most important information I should know about TIROSINT-SOL?
Do not use TIROSINT-SOL to treat weight problems or weight loss.

What is TIROSINT-SOL?

TIROSINT-SOL is a prescription medicine that contains a hormone called levothyroxine which is normally produced by the thyroid gland. TIROSINT-SOL is used:

- to replace or give extra levothyroxine in people whose thyroid does not produce enough of this hormone; or
- with surgery and radiodine therapy to manage a type of thyroid cancer called thyroid-dependent well-differentiated thyroid cancer.

TIROSINT-SOL should not be used to treat people who are recovering from swelling of the thyroid gland (thyroiditis) and whose bodies do not produce enough levothyroxine for a short time.

Do not take TIROSINT-SOL:

- if you are allergic to glycerol the inactive ingredient in TIROSINT-SOL; or
- if your adrenal glands are not working well and you have not been treated for this problem.

Before you take TIROSINT-SOL, tell your doctor about all of your medical conditions, including if you:

- have or have had heart problems
- have or have had thyroid nodules
- have adrenal or pituitary gland problems
- have any food or drug allergies
- have low red blood cell count (anemia)
- have diabetes
- have weak bones (osteoporosis)
- have or had a history of blood clotting problems
- have recently received radiation therapy with iodine (such as I-131)
- are pregnant or plan to become pregnant. Your doctor may need to change your TIROSINT-SOL dose while you are pregnant.
- are breastfeeding. TIROSINT-SOL can pass into your milk. Talk to your doctor about the best way to feed your baby if you take TIROSINT-SOL.

Tell your doctor about all the medicines you are taking including prescription and over-the-counter medicines, vitamins and herbal supplements. TIROSINT-SOL may affect the way other medicines work, and other medicines may affect how TIROSINT-SOL works so your doctor may have to adjust the amount of medicines you take. You can ask your doctor or pharmacist for a list of medicines that interact with TIROSINT-SOL.

How should I take TIROSINT-SOL?

- TIROSINT-SOL is for oral use only. Do not inhale, inject, or place TIROSINT-SOL in the eyes.
- See the detailed " Instructions for Use" that come with TIROSINT-SOL for information on the right way to take your dose of TIROSINT-SOL oral solution.
- Take TIROSINT-SOL exactly as your doctor tells you to take it.
- Your doctor will tell you how much TIROSINT-SOL to take each day.
- Your doctor may change your dose, if needed.
- Take your dose of TIROSINT-SOL 1 time each day 15 minutes before breakfast on an empty stomach.
- Certain medicines can interfere with how TIROSINT-SOL is absorbed by your body. Take TIROSINT-SOL:
  - at least 4 hours before or after you take medicines that contain calcium carbonate or iron (ferrous sulfate); and
  - at least 4 hours before you take medicines that contain bile acid sequestrants or ion exchange resins.
    Know the medicines you take. Ask your doctor or pharmacist for a list of these medicines, if you are not sure.
- Certain foods including soybean flour, cotton seed meal, walnuts, and dietary fiber can affect your treatment and dose of TIROSINT-SOL. Talk to your doctor if you eat or drink these foods.
- Do not remove TIROSINT–SOL ampules from the sealed aluminum foil pouch until you are ready to use them .
- Use all 5 TIROSINT-SOL ampules within three (3) months after opening the aluminum foil pouch.
- Your doctor should do certain blood tests while you are taking TIROSINT-SOL and may change your daily dose of TIROSINT-SOL as needed. Keep taking TIROSINT-SOL unless your doctor tells you to stop or to change your dose.

It may take weeks before you notice your symptoms getting better. Keep using this medicine even if you feel well. If you take too much TIROSINT-SOL, call your doctor, your Poison Control Center at 1-800-222-1222, or go to the nearest hospital emergency room right away.

What are the possible side effects of TIROSINT-SOL?
TIROSINT-SOL may cause serious side effects, including:

- heart problems. You may experience an increased heart rate, chest pain and irregular heartbeat. Your risk of developing heart problems may be greater if you are elderly, you have heart problems, or you take too much TIROSINT-SOL. Your doctor may reduce your dose or stop treatment with TIROSINT-SOL for a while if you develop heart problems.
- worsening diabetic control. If you are diabetic, it may be harder to control your blood sugar levels causing hyperglycemia while taking TIROSINT-SOL. Check your blood sugar levels closely after starting, changing, or stopping treatment with TIROSINT-SOL. Your doctor may have to change your diabetes treatment plan.
- weak or brittle bones. Your risk of developing weak or brittle bones may be greater if you are post-menopausal or you take too much TIROSINT-SOL.

The most common side effects of TIROSINT-SOL include:

- fast or irregular heartbeat
- chest pain
- shortness of breath
- leg cramps
- headache
- nervousness
- hives or skin rash

- irritability
- sleep problems (insomnia)
- tremors
- muscle weakness
- change in appetite
- weight loss

- vomiting
- diarrhea
- sweating a lot
- heat intolerance
- fever
- changes in menstrual period

Other side effects may include partial hair loss during the first months of treatment with TIROSINT-SOL. This usually lasts a short period of time (temporary).

These are not all the possible side effects of TIROSINT-SOL. Call your doctor for medical advice about side effects. You may report side effects to IBSA Pharma Inc. at 1-800-587-3513 or FDA at 1-800-FDA-1088.

How should I store TIROSINT-SOL?

- Store TIROSINT-SOL at room temperature between 68°F to 77°F (20°C to 25°C).
- Use TIROSINT-SOL within three (3) months after opening the pouch. Keep TIROSINT-SOL in the original closed pouch until you are ready to use it as important information may be lost (i.e., manufacturer/distributor names and distributor contact phone number.
- Do not store the diluted or mixed TIROSINT-SOL solution.

Keep TIROSINT-SOL and all medicines out of the reach of children.

General information about the safe and effective use of TIROSINT-SOL

Medicines are sometimes prescribed for purposes other than those listed in a Patient Information leaflet. Do not use TIROSINT-SOL for a condition for which it was not prescribed. Do not give TIROSINT-SOL to other people, even if they have the same symptoms as you. It may harm them. You can ask your pharmacist or doctor for information about TIROSINT-SOL that is written for health professionals.

What are the ingredients in TIROSINT- SOL oral solution?
Active ingredient: levothyroxine sodium
Inactive ingredients: glycerol, and water
Manufactured by: IBSA Institut Biochimique SA, 6912 Pazzallo, Switzerland
Marketed and distributed by: IBSA Pharma Inc, Parsippany, NJ 07054 USA
For more information, go to www.tirosintsol.com or call 1-800-587-3513.

This Patient Information has been approved by the U.S. Food and Drug Administration

Issued: 07/2024

Instructions for Use
TIROSINT®-SOL (tee-row-sent-sōl)
(levothyroxine sodium)
oral solution

Read this Instructions for Use before you start taking TIROSINT-SOL and each time you get a refill. There may be new information. This leaflet does not take the place of talking to your healthcare provider about your medical condition or treatment.

Important Information:

- TIROSINT-SOL is for oral use only. Do not inhale, inject, or place TIROSINT-SOL in the eyes.
- TIROSINT-SOL can be taken:
  - by diluting or mixing in water first or
  - by directly squeezing into the mouth or onto a spoon.
- Do not dilute or mix TIROSINT-SOL with any liquid other than water.
- Open the ampule and prepare the solution right before you take TIROSINT-SOL.
- After you have diluted or mixed TIROSINT-SOL it must be taken or thrown away.

Step 1. Using scissors, open the aluminum pouch by cutting the edge along the dotted line (See Figure A) .

Figure A

Step 2. Remove 1 ampule from the strip to be used right away (See Figure B) . Return the unused ampules back into the pouch before storing.

Figure B

Step 3. Hold the TIROSINT-SOL ampule upright (cap on top) between the first finger and thumb without squeezing the ampule. Open the ampule by twisting off the top (See Figure C) .

Figure C

Step 4.

Taking TIROSINT-SOL by diluting or mixing:

- Turn the ampule upside down.
- Squeeze the middle, softer part of the ampule between the first finger and thumb slowly to release the liquid medicine into a glass or cup containing water, then release the pressure and wait a few seconds (See Figure D).
- Keeping the ampule upside down, repeat this step for a minimum of 5 times, until no more liquid medicine comes out of the ampule.
- Stir the solution.
- Drink all the liquid medicine right away.
- Rinse the glass or cup with more water and drink to make sure all the medicine has been taken.

Figure D

Taking TIROSINT-SOL directly into the mouth or by spoon:

- Turn the ampule upside down.
- Squeeze the middle, softer part of the ampule between the first finger and thumb slowly to release the liquid medicine into the mouth or onto a spoon, then release the pressure and wait a few seconds (See Figure E).
- Keeping the ampule upside down, repeat this step for a minimum of 5 times, until no more liquid medicine comes out of the ampule.

Figure E

Step 5. Throw away (discard) the empty ampule.

How should I store TIROSINT-SOL?

- Store TIROSINT-SOL at room temperature between 68°F to 77°F (20°C to 25°C).
- Use TIROSINT-SOL within three (3) months after opening the pouch. Keep TIROSINT-SOL in the original closed pouch until you are ready to use it as important information may be lost (i.e., manufacturer/distributor names and distributor contact phone number.
- Do not store the diluted or mixed TIROSINT-SOL solution.

Keep TIROSINT-SOL and all medicines out of the reach of children.

This Instructions for Use has been approved by the U.S. Food and Drug Administration.

Manufacturer: IBSA Institut Biochimique SA, 6912 Pazzallo, Switzerland
Marketed and Distributed by: IBSA Pharma Inc., Parsippany, NJ 07054 USA

Issued: July 2024

FI/169 (USA) 5000003397 Rev. 06 06.24

PRINCIPAL DISPLAY PANEL - 13 microgram/mL Ampule Pouch Carton

NDC 71858-0105-5

TIROSINT® - SOL
(levothyroxine sodium) Oral Solution

13 microgram/mL

For Oral Use Only – NOT for Inhalation, Injection or Ophthalmic Use

Rx Only

6 pouches x 5 ampules

IBSA

PRINCIPAL DISPLAY PANEL - 25 microgram/mL Ampule Pouch Carton

NDC 71858-0110-5

TIROSINT® - SOL
(levothyroxine sodium) Oral Solution

25 microgram/mL

For Oral Use Only – NOT for Inhalation, Injection or Ophthalmic Use

Rx Only

6 pouches x 5 ampules

IBSA

PRINCIPAL DISPLAY PANEL - 37.5 microgram/mL Ampule Pouch Carton

NDC 71858-0112-5

TIROSINT® - SOL
(levothyroxine sodium) Oral Solution

37.5 microgram/mL

For Oral Use Only – NOT for Inhalation, Injection or Ophthalmic Use

Rx Only

6 pouches x 5 ampules

IBSA

PRINCIPAL DISPLAY PANEL - 44 microgram/mL Ampule Pouch Carton

NDC 71858-0113-5

TIROSINT® - SOL
(levothyroxine sodium) Oral Solution

44 microgram/mL

For Oral Use Only – NOT for Inhalation, Injection or Ophthalmic Use

Rx Only

6 pouches x 5 ampules

IBSA

PRINCIPAL DISPLAY PANEL - 50 microgram/mL Ampule Pouch Carton

NDC 71858-0115-5

TIROSINT® - SOL
(levothyroxine sodium) Oral Solution

50 microgram/mL

For Oral Use Only – NOT for Inhalation, Injection or Ophthalmic Use

Rx Only

6 pouches x 5 ampules

IBSA

PRINCIPAL DISPLAY PANEL - 62.5 microgram/mL Ampule Pouch Carton

NDC 71858-0117-5

TIROSINT® - SOL
(levothyroxine sodium) Oral Solution

62.5 microgram/mL

For Oral Use Only – NOT for Inhalation, Injection or Ophthalmic Use

Rx Only

6 pouches x 5 ampules

IBSA

PRINCIPAL DISPLAY PANEL - 75 microgram/mL Ampule Pouch Carton

NDC 71858-0120-5

TIROSINT® - SOL
(levothyroxine sodium) Oral Solution

75 microgram/mL

For Oral Use Only – NOT for Inhalation, Injection or Ophthalmic Use

Rx Only

6 pouches x 5 ampules

IBSA

PRINCIPAL DISPLAY PANEL - 88 microgram/mL Ampule Pouch Carton

NDC 71858-0125-5

TIROSINT® - SOL
(levothyroxine sodium) Oral Solution

88 microgram/mL

For Oral Use Only – NOT for Inhalation, Injection or Ophthalmic Use

Rx Only

6 pouches x 5 ampules

IBSA

PRINCIPAL DISPLAY PANEL - 100 microgram/mL Ampule Pouch Carton

NDC 71858-0130-5

TIROSINT® - SOL
(levothyroxine sodium) Oral Solution

100 microgram/mL

For Oral Use Only – NOT for Inhalation, Injection or Ophthalmic Use

Rx Only

6 pouches x 5 ampules

IBSA

PRINCIPAL DISPLAY PANEL - 112 microgram/mL Ampule Pouch Carton

NDC 71858-0135-5

TIROSINT® - SOL
(levothyroxine sodium) Oral Solution

112 microgram/mL

For Oral Use Only – NOT for Inhalation, Injection or Ophthalmic Use

Rx Only

6 pouches x 5 ampules

IBSA

PRINCIPAL DISPLAY PANEL - 125 microgram/mL Ampule Pouch Carton

NDC 71858-0140-5

TIROSINT® - SOL
(levothyroxine sodium) Oral Solution

125 microgram/mL

For Oral Use Only – NOT for Inhalation, Injection or Ophthalmic Use

Rx Only

6 pouches x 5 ampules

IBSA

PRINCIPAL DISPLAY PANEL - 137 microgram/mL Ampule Pouch Carton

NDC 71858-0145-5

TIROSINT® - SOL
(levothyroxine sodium) Oral Solution

137 microgram/mL

For Oral Use Only – NOT for Inhalation, Injection or Ophthalmic Use

Rx Only

6 pouches x 5 ampules

IBSA

PRINCIPAL DISPLAY PANEL - 150 microgram/mL Ampule Pouch Carton

NDC 71858-0150-5

TIROSINT® - SOL
(levothyroxine sodium) Oral Solution

150 microgram/mL

For Oral Use Only – NOT for Inhalation, Injection or Ophthalmic Use

Rx Only

6 pouches x 5 ampules

IBSA

PRINCIPAL DISPLAY PANEL - 175 microgram/mL Ampule Pouch Carton

NDC 71858-0155-5

TIROSINT® - SOL
(levothyroxine sodium) Oral Solution

175 microgram/mL

For Oral Use Only – NOT for Inhalation, Injection or Ophthalmic Use

Rx Only

6 pouches x 5 ampules

IBSA

PRINCIPAL DISPLAY PANEL - 200 microgram/mL Ampule Pouch Carton

NDC 71858-0160-5

TIROSINT® - SOL
(levothyroxine sodium) Oral Solution

200 microgram/mL

For Oral Use Only – NOT for Inhalation, Injection or Ophthalmic Use

Rx Only

6 pouches x 5 ampules

IBSA